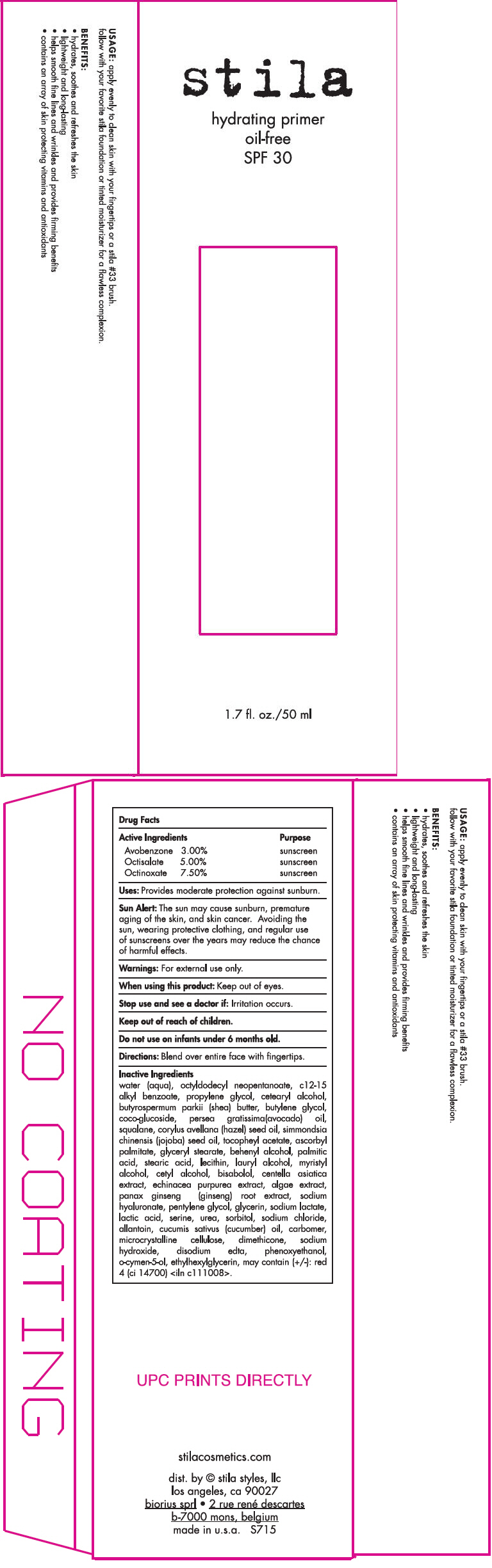 DRUG LABEL: Stila Hydrating Primer Oil-Free SPF 30 
NDC: 76049-715 | Form: LOTION
Manufacturer: Stila Styles, LLC
Category: otc | Type: HUMAN OTC DRUG LABEL
Date: 20131118

ACTIVE INGREDIENTS: Avobenzone 3 mg/1 mL; Octisalate 5 mg/1 mL; Octinoxate 7.5 mg/1 mL
INACTIVE INGREDIENTS: water; octyldodecyl neopentanoate; alkyl (c12-15) benzoate; propylene glycol; cetostearyl alcohol; shea butter; butylene glycol; coco glucoside; avocado oil; squalane; european hazelnut oil; jojoba oil; .alpha.-tocopherol acetate; ascorbyl palmitate; glyceryl monostearate; docosanol; palmitic acid; stearic acid; lauryl alcohol; myristyl alcohol; cetyl alcohol; levomenol; centella asiatica; echinacea purpurea; asian ginseng; hyaluronate sodium; pentylene glycol; glycerin; sodium lactate; lactic acid; serine; urea; sorbitol; sodium chloride; allantoin; cucumber seed oil; cellulose, microcrystalline; dimethicone; sodium hydroxide; edetate disodium; phenoxyethanol; o-cymen-5-ol; ethylhexylglycerin; fd&c red no. 4

Stila Hydrating Primer Oil-Free SPF 30
(All Shades)

ACTIVE INGREDIENT

Active Ingredients |  |  | Purpose
Avobenzone | 3.00% |  | sunscreen
Octisalate | 5.00% |  | sunscreen
Octinoxate | 7.50% |  | sunscreen

Uses

Provides moderate protection against sunburn.

Sun Alert

The sun may cause sunburn, premature aging of the skin, and skin cancer. Avoiding the sun, wearing protective clothing, and regular use of sunscreens over the years may reduce the chance of harmful effects.

Warnings

For external use only.

When using this product

Keep out of eyes.

Stop use and see a doctor if

Irritation occurs.

Keep out of reach of children.

Do not use on infants under 6 months old.

Directions

Blend over entire face with fingertips.

Inactive Ingredients

water (aqua), octyldodecyl neopentanoate, c12-15 alkyl benzoate, propylene glycol, cetearyl alcohol, butyrospermum parkii (shea) butter, butylene glycol, coco-glucoside, persea gratissima(avocado) oil, squalane, corylus avellana (hazel) seed oil, simmondsia chinensis (jojoba) seed oil, tocopheyl acetate, ascorbyl palmitate, glyceryl stearate, behenyl alcohol, palmitic acid, stearic acid, lecithin, lauryl alcohol, myristyl alcohol, cetyl alcohol, bisabolol, centella asiatica extract, echinacea purpurea extract, algae extract, panax ginseng (ginseng) root extract, sodium hyaluronate, pentylene glycol, glycerin, sodium lactate, lactic acid, serine, urea, sorbitol, sodium chloride, allantoin, cucumis sativus (cucumber) oil, carbomer, microcrystalline cellulose, dimethicone, sodium hydroxide, disodium edta, phenoxyethanol, o-cymen-5-ol, ethylhexylglycerin, may contain (+/-): red 4 (ci 14700) <iln c111008>.

dist. by © stila styles, llc
los angeles, ca 90027

PRINCIPAL DISPLAY PANEL - 50 ml Tube Carton

stila

hydrating primer
oil-free
SPF 30

1.7 fl. oz./50 ml